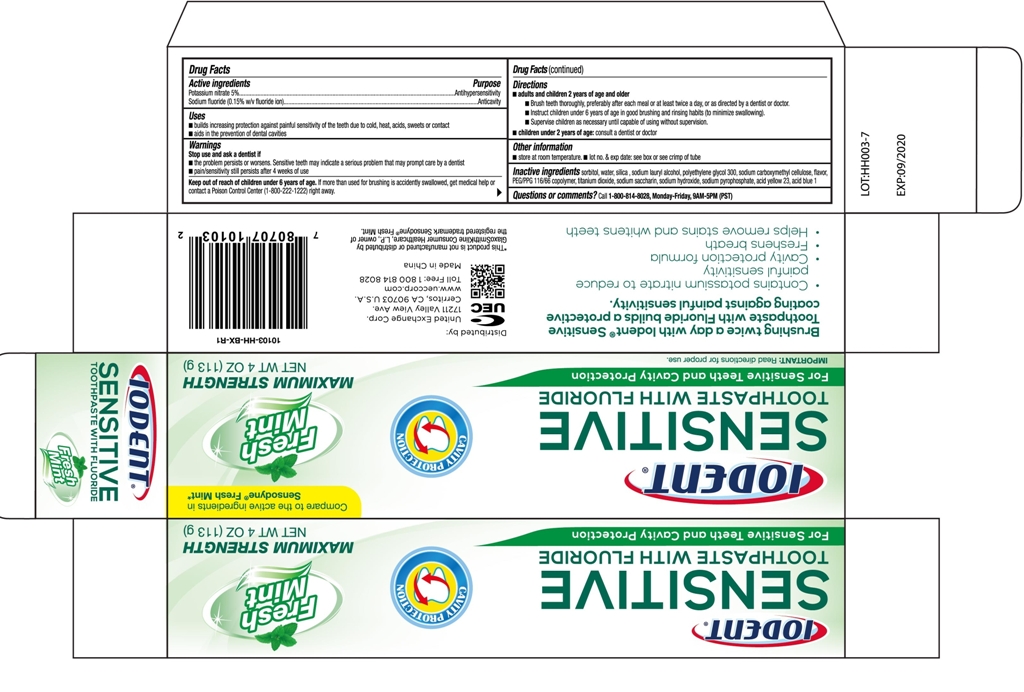 DRUG LABEL: IODENT SENSITIVE
NDC: 72129-002 | Form: PASTE
Manufacturer: Zhaoqing Longda Biotechnology Co., Ltd.
Category: otc | Type: HUMAN OTC DRUG LABEL
Date: 20220215

ACTIVE INGREDIENTS: SODIUM FLUORIDE 0.15 g/100 g; POTASSIUM NITRATE 5 g/100 g
INACTIVE INGREDIENTS: SODIUM PYROPHOSPHATE; TITANIUM DIOXIDE; WATER; SODIUM SILICATE; SODIUM HYDROXIDE; SODIUM LAURYL SULFATE; POLYETHYLENE GLYCOL 300; SODIUM CARBOXYMETHYL .BETA.-GLUCAN (DS 0.65-0.85); POTASSIUM SODIUM SACCHARATE; SORBITOL; PEG/PPG-116/66 COPOLYMER

72129 002 Potassium Nitrate Sodium Fluoride

Active Ingredient

Potassium Nitrate 5%

Sodium Fluoride . 0.15%

Purpose

Antihypersensitivity

Anticavity

Use

Builds increasing protection against painful sensitivity of the teeth due to cold , heat , acids, sweets or contact.

Aids in the prevention of dental cavities

Warning

Stop use and ask a dentist if

The problem persists or worsens. Sensitive teeth may indicate a serious problem that may prompt care by a dentist

Pain/sensitivity still persists after 4 weeks of use

Directions

Adults and children 12 years of age and older

Apply at least at 1-inch strip of product onto a soft bristle toothbrush

Brush teeth thoroughly for at least 1 minute twice a day(morning and evening), and not more than 3 times a day, or as recommended by a dentist or doctor. Make sure to brush all sensitive areas of the teeth. Minimize swallowing , Spit out after brushing.

Children under 12 years of age:consult a dentist or doctor

Inactive Ingredients

calcium carbonate , water, sorbitol , silica, polyethylene glycol 400, sodium laury alcohol, sodium carboxymethyl cellulose, flavor, sodium saccharin, methylparaben, propyparaben , sodium hydroxide

Keep out of reach of children under 6 years of age

Keep out of reach of children. If more than used for brushing is accidentally swallowed, get medical help or contact a Poison Control Center right away